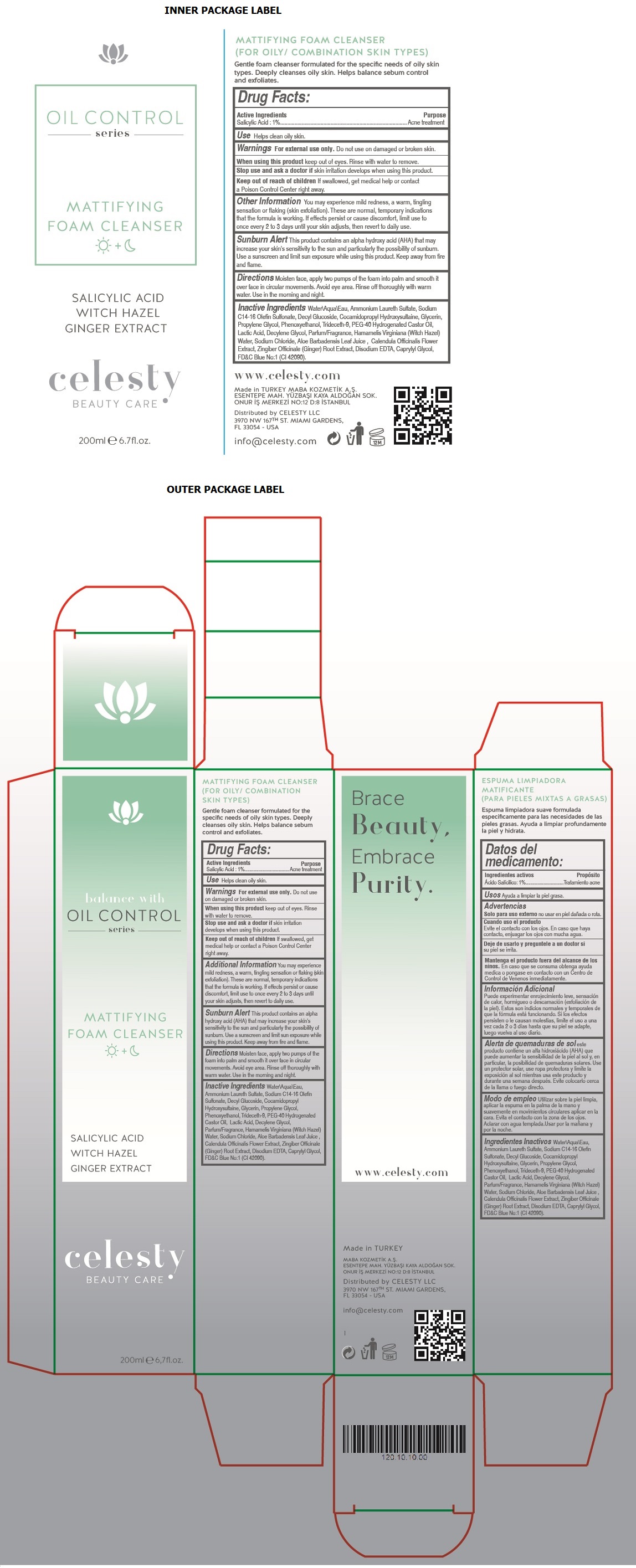 DRUG LABEL: Celesty
NDC: 81120-107 | Form: LOTION
Manufacturer: MABA KOZMETIK LIMITED SIRKETI
Category: otc | Type: HUMAN OTC DRUG LABEL
Date: 20201210

ACTIVE INGREDIENTS: SALICYLIC ACID 1 g/100 mL
INACTIVE INGREDIENTS: WATER; AMMONIUM LAURETH-2 SULFATE; SODIUM C14-16 OLEFIN SULFONATE; DECYL GLUCOSIDE; COCAMIDOPROPYL HYDROXYSULTAINE; GLYCERIN; PROPYLENE GLYCOL; PHENOXYETHANOL; TRIDECETH-9; POLYOXYL 40 HYDROGENATED CASTOR OIL; LACTIC ACID, UNSPECIFIED FORM; DECYLENE GLYCOL; HAMAMELIS VIRGINIANA TOP WATER; SODIUM CHLORIDE; ALOE VERA LEAF; CALENDULA OFFICINALIS FLOWER; GINGER; EDETATE DISODIUM ANHYDROUS; CAPRYLYL GLYCOL; FD&C BLUE NO. 1

celesty OIL CONTROL series MATTIFYING FOAM CLEANSER

Active Ingredients

Salicylic Acid : 1%

Purpose

Acne treatment

Use

Helps clean oily skin.

Warnings

For external use only. Do not use on damaged or broken skin.

When using this product keep out of eyes. Rinse with water to remove.

Stop use and ask a doctor if skin irritation develops when using this product.

Keep out of reach of children If swallowed, get medical help or contact a Poison Control Center right away.

Additional Information

You may experience mild redness, a warm, tingling sensation or flaking (skin exfoliation). These are normal, temporary indications that the formula is working. If effects persist or cause discomfort, limit use to once every 2 to 3 days until your skin adjusts, then revert to daily use.

Sunburn Alert This product contains an alpha hydroxy acid (AHA) that may increase your skin's sensitivity to the sun and particularly the possibility of sunburn. Use a sunscreen and limit sun exposure while using this product. Keep away from fire and flame.

Directions

Moisten face, apply two pumps of the foam into palm and smooth it over face in circular movements. Avoid eye area. Rinse off thoroughly with warm water. Use in the morning and night.

Inactive Ingredients

Water\Aqua\Eau, Ammonium Laureth Sulfate, Sodium C14-16 Olefin Sulfonate, Decyl Glucoside, Cocamidopropyl Hydroxysultaine, Glycerin, Propylene Glycol, Phenoxyethanol, Trideceth-9, PEG-40 Hydrogenated Castor Oil, Lactic Acid, Decylene Glycol, Parfum/Fragrance, Hamamelis Virginiana (Witch Hazel) Water, Sodium Chloride, Aloe Barbadensis Leaf Juice, Calendula Officinalis Flower Extract, Zingiber Officinale (Ginger) Root Extract, Disodium EDTA, Caprylyl Glycol, FD&C Blue No:1 (CI 42090)

balance with OIL CONTROL series

SALICYLIC ACID

WITCH HAZEL

GINGER EXTRACT

BEAUTY CARE

(FOR OILY/ COMBINATION SKIN TYPES)

Gentle foam cleanser formulated for the specific needs of oily skin types. Deeply cleanses oily skin. Helps balance sebum control and exfoliates.

Brace Beauty, Embrace Purity.

www.celesty.com

Made in TURKEY

MABA KOZMETIK A.S.

ESENTEPE MAH. YUZBASI KAYA ALDOGAN SOK.

ONUR IS MERKEZI NO:12 D:8 ISTANBUL

Distributed by CELESTY LLC

3970 NW 167TH ST. MIAMI GARDENS,

FL 33054 - USA

info@celesty.com